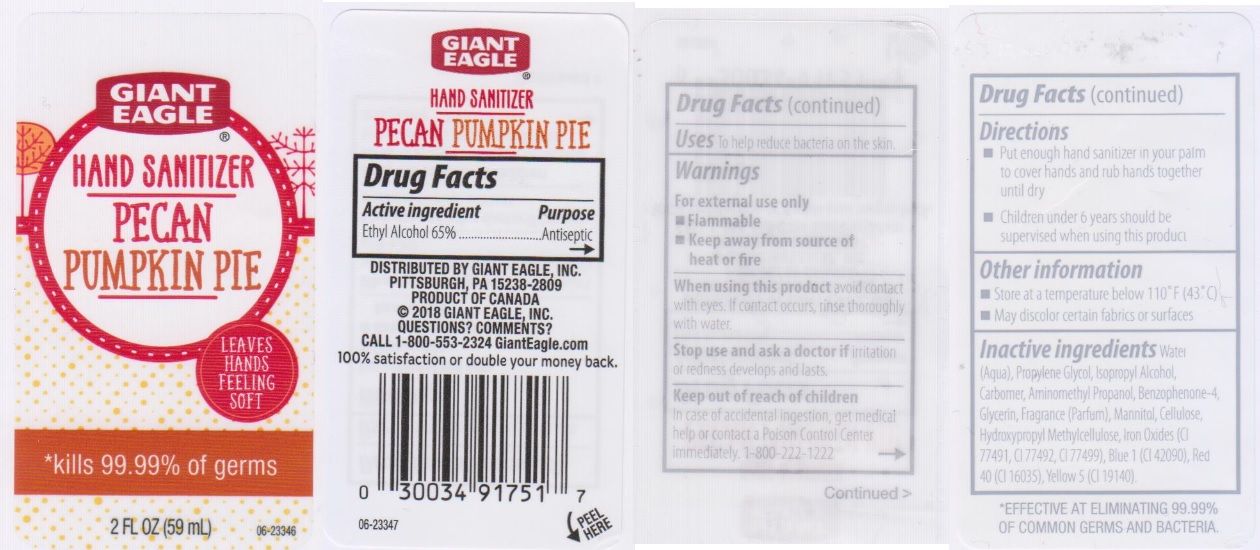 DRUG LABEL: Giant Eagle Pecan Pumpkin Pie Hand Sanitizer
NDC: 63148-015 | Form: LIQUID
Manufacturer: Apollo Health and Beauty Care Inc.
Category: otc | Type: HUMAN OTC DRUG LABEL
Date: 20180620

ACTIVE INGREDIENTS: ALCOHOL 650 mg/1 mL
INACTIVE INGREDIENTS: WATER; PROPYLENE GLYCOL; ISOPROPYL ALCOHOL; CARBOMER 934; AMINOMETHYLPROPANOL; SULISOBENZONE; GLYCERIN; MANNITOL; POWDERED CELLULOSE; HYPROMELLOSES; FERRIC OXIDE RED; FERRIC OXIDE YELLOW; FERROSOFERRIC OXIDE; FD&C BLUE NO. 1; FD&C RED NO. 40; FD&C YELLOW NO. 5

Drug Facts

Active ingredient

Ethyl Alcohol 65%

Purpose

Antiseptic

Uses

To help reduce bacteria on the skin.

Warnings

For external use only

- Flammable
- Keep away from source of heat or fire

When using this product

avoid contact with eyes. If contact occurs, rinse thoroughly with water.

Stop use and ask a doctor if

irritation or redness develops and lasts.

Keep out of reach of children.

In case of accidental ingestion, get medical help or contact a Poison Control Center immediately. 1-800-222-1222

Directions

- Put enough hand sanitizer in your palm to cover hands and rub hands together until dry.
- Children under 6 years should be supervised when using this product.

Other information

- Store at a temperature below 110°F (43°C)
- May discolor certain fabrics or surfaces

Inactive ingredients

Water (Aqua), Propylene Glycol, Isopropyl Alcohol, Carbomer, Aminomethyl Propanol, Benzophenone-4, Glycerin, Fragrance (Parfum), Mannitol, Cellulose, Hydroxyethylcellulose, Iron Oxides (CI 77491, CI 77492, CI 77499), Blue 1 (CI 42090), Red 40 (CI 16035), Yellow 5 (CI 19140).